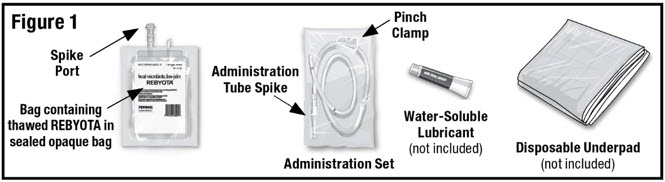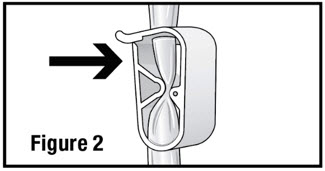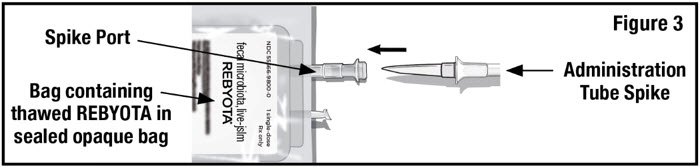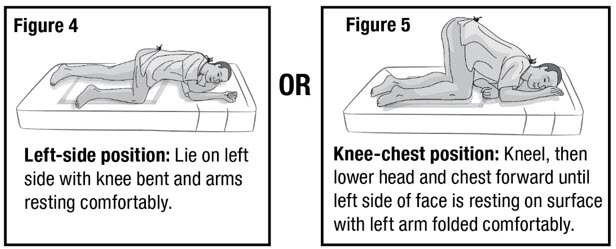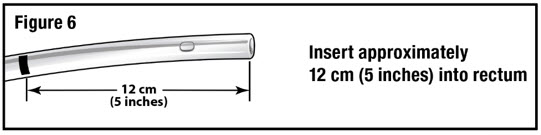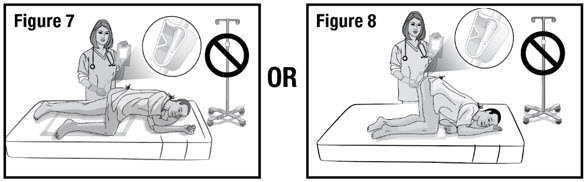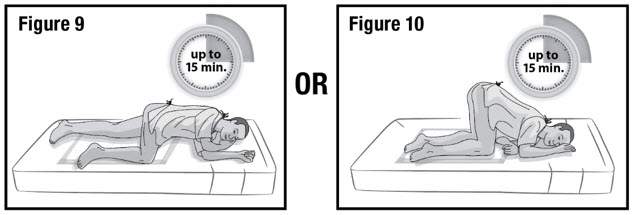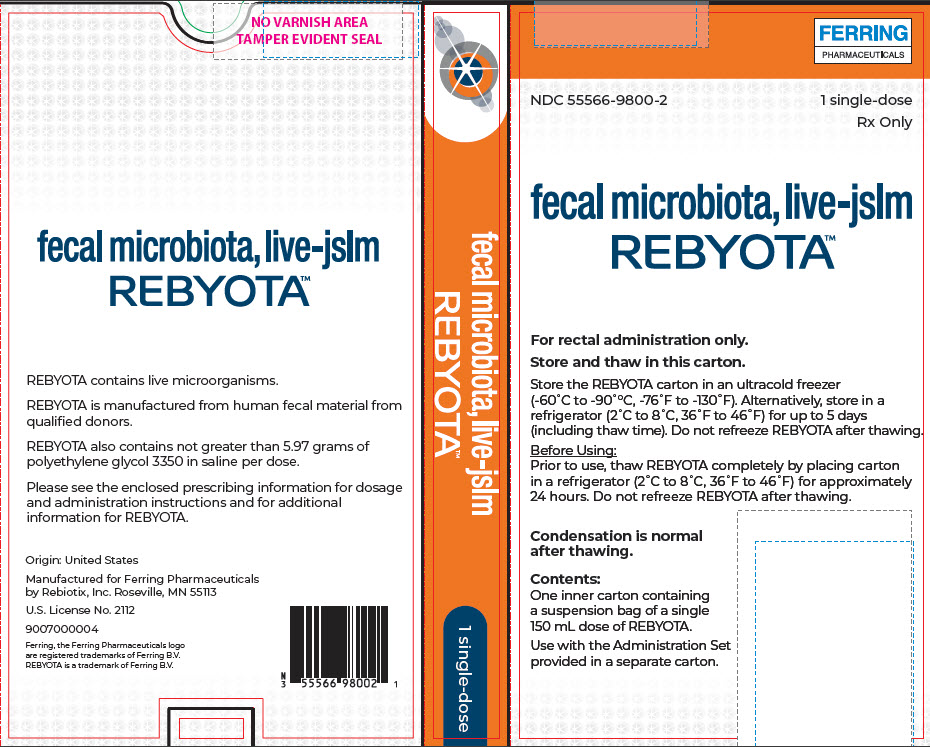 DRUG LABEL: Rebyota
NDC: 55566-9800 | Form: SUSPENSION
Manufacturer: Ferring Pharmaceuticals Inc.
Category: prescription | Type: HUMAN PRESCRIPTION DRUG LABEL
Date: 20241223

ACTIVE INGREDIENTS: Donor Human Stool 50000000000 [CFU]/150 mL

HIGHLIGHTS OF PRESCRIBING INFORMATION

These highlights do not include all the information needed to use REBYOTA safely and effectively. See full prescribing information for REBYOTA.
REBYOTA™ (fecal microbiota, live - jslm) suspension, for rectal use
Initial U.S. Approval: 2022

1 INDICATIONS AND USAGE

REBYOTA is indicated for the prevention of recurrence of Clostridioides difficile infection (CDI) in individuals 18 years of age and older, following antibiotic treatment for recurrent CDI. (1)

Limitation of Use:
REBYOTA is not indicated for treatment of CDI.

2 DOSAGE AND ADMINISTRATION

For rectal administration only.

Administer REBYOTA 24 to 72 hours after the last dose of antibiotics for CDI. (2)

Administer a single dose of 150 mL rectally of REBYOTA. (2)

3 DOSAGE FORMS AND STRENGTHS

Suspension. A single dose is 150 mL. (3)

4 CONTRAINDICATIONS

Severe allergic reactions (e.g. anaphylaxis) to any component of REBYOTA. (4)

6 ADVERSE REACTIONS

The most commonly reported (≥ 3%) adverse reactions occurring in adults following a single dose of REBYOTA were abdominal pain, (8.9%), diarrhea (7.2%), abdominal distention (3.9%), flatulence (3.3%), and nausea (3.3%) (Table 1).

To report SUSPECTED ADVERSE REACTIONS, contact Ferring Pharmaceuticals Inc. at 1-888-FERRING (1-888-337-7464) or FDA at 1-800-FDA-1088 or www.fda.gov/medwatch. (6)

FULL PRESCRIBING INFORMATION

1 INDICATIONS AND USAGE

REBYOTA is indicated for the prevention of recurrence of Clostridioides difficile infection (CDI) in individuals 18 years of age and older following antibiotic treatment for recurrent CDI.

Limitation of Use:

REBYOTA is not indicated for treatment of CDI.

2 DOSAGE AND ADMINISTRATION

For rectal administration only.

2.1 Dose

A single dose is 150 mL.

2.2 Preparation

Prior to use, thaw REBYOTA completely by placing the carton in a refrigerator, 2°C to 8°C (36°F to 46°F), for approximately 24 hours. REBYOTA carton may be stored in the refrigerator at 2°C to 8°C (36°F to 46°F) and used within 5 days, including thawing time.

DO NOT thaw using a heat source such as a microwave or hot water.

Condensation is normal after thawing.

Remove the thawed REBYOTA carton from the refrigerator. Remove the bag containing thawed REBYOTA from the outer carton and the inner carton insert. DO NOT remove the bag containing thawed REBYOTA from the sealed outer bag. Locate an Administration Set (supplied), water-soluble lubricant (not included) and a disposable underpad (not included) (See Figure 1).

1. Open the administration set and close the pinch clamp by pushing the clamp until it is fully closed (see Figure 2).
2. Remove the tab from the spike port of the bag containing thawed REBYOTA and remove the cap from the administration tube spike. Insert the administration tube spike through the spike port of the bag containing thawed REBYOTA (see Figure 3).

DO NOT remove air from the administration tube prior to insertion to avoid loss of REBYOTA.

2.3 Administration

Administer REBYOTA 24 to 72 hours after the last dose of antibiotics for CDI.

1. Prepare the patient for administration by requesting they empty their bladder and bowel, if possible. Place the patient in the left-side position or the knee-chest position with a disposable underpad beneath the patient (see Figures 4 and 5).
2. Apply water-soluble lubricant to the administration tube tip. Gently insert the administration tube tip into the rectum about 12 cm (5 inches) in a direction pointed slightly toward the navel (umbilicus) (see Figure 6).
3. Hold the administration tube in place with one hand for the entire procedure to maintain the tube position in the rectum. With the other hand, open the pinch clamp on the administration tube, and then gradually raise the bag to allow delivery of REBYOTA via gravity flow (see Figure 7 and 8).

DO NOT allow the administration tube to sag or loop as this will prevent the entire dose from being delivered.

DO NOT squeeze the bag to deliver REBYOTA as this could be uncomfortable for the patient.

DO NOT hang the bag from an IV stand.

4. When the entire dose has been delivered, close the pinch clamp and then slowly withdraw the tube. Take care to prevent any residual REBYOTA remaining in the tube from leaking out.

NOTE: Some REBYOTA will remain in the tube after administration.

5. Keep the patient in the left-side position or the knee-chest position for up to 15 minutes to minimize any cramping that may occur (see Figure 9 and 10). There are no restrictions on the patient's use of the restroom.

Dispose of all components in medical waste.

3 DOSAGE FORMS AND STRENGTHS

Suspension. A single dose is 150 mL.

4 CONTRAINDICATIONS

Do not administer REBYOTA to individuals with a history of a severe allergic reaction (e.g. anaphylaxis) to any of the known product components [see Description 11].

5 WARNINGS AND PRECAUTIONS

5.1 Transmissible infectious agents

Because REBYOTA is manufactured from human fecal matter it may carry a risk of transmitting infectious agents. Any infection suspected by a physician possibly to have been transmitted by this product should be reported by the physician or other healthcare provider to Ferring Pharmaceuticals Inc.

5.2 Management of acute allergic reactions

Appropriate medical treatment must be immediately available in the event an acute anaphylactic reaction occurs following administration of REBYOTA.

5.3 Potential presence of food allergens

REBYOTA is manufactured from human fecal matter and may contain food allergens. The potential for REBYOTA to cause adverse reactions due to food allergens is unknown.

6 ADVERSE REACTIONS

The most commonly reported (≥ 3%) adverse reactions occurring in adults following a single dose of REBYOTA were abdominal pain, (8.9%), diarrhea (7.2%), abdominal distention (3.9%), flatulence (3.3%), and nausea (3.3%).

6.1 Clinical Trials Experience

Because clinical trials are conducted under widely varying conditions, adverse reaction rates observed in the clinical trials of a drug cannot be directly compared to rates in the clinical trials of another drug and may not reflect the rates observed in practice.

The safety of REBYOTA was evaluated in 2 randomized, double-blind clinical studies (Study 1: NCT03244644 and Study 2: NCT02299570) and 3 open-label clinical studies (NCT01925417, NCT02589847, NCT03931941) conducted in the United States and Canada. A total of 978 adults 18 years of age and older with a history of 1 or more recurrences of Clostridioides difficile (CDI) infection and whose symptoms were controlled 24 – 72 hours post-antibiotic treatment were enrolled and received 1 or more doses of REBYOTA; 595 of whom received a single dose of REBYOTA. In the 2 randomized, double-blind clinical studies, 131 adults were originally randomized to receive placebo and 48 crossed over to receive an open-label dose of REBYOTA after additional CDI recurrence. Overall, across the 5 studies, the median age of participants was 64 years and 67.2 % were female. The racial and ethnic distribution was as follows: 93.8% were white, and 2.4% were of Hispanic or Latino ethnicity. No meaningful differences in demographic characteristics occurred across the treatment groups. Study 1 and Study 2 excluded individuals with celiac disease, Inflammatory Bowel Disease, Irritable Bowel Syndrome, and chronic diarrhea. Individuals with these conditions were not excluded from one of the open-label studies (NCT03931941), and individuals with food allergies were not excluded from any of the 5 clinical studies.

Adverse Reactions

Across the 5 clinical studies, participants recorded solicited adverse events in a diary for the first 7 days after each dose of REBYOTA or placebo. Participants were monitored for all other adverse events by queries during scheduled visits, with duration of follow-up ranging from 6 to 24 months after the last dose. In Study 1, a multi-center, double-blind randomized (2:1), placebo-controlled trial conducted in the United States and Canada, 180 adults 18 years of age and older received a single dose of REBYOTA and 87 received placebo. Participants with a recurrence of CDI (rCDI) during the first 8 weeks after receipt of REBYOTA or placebo were censored from analysis at the time of rCDI. During the first two weeks following a dose of REBYOTA or placebo, 34 participants (18.9%) and 24 participants (27.6%) respectively, were censored. Overall, during the 8 week follow up period, 47 REBYOTA recipients (26.1%) and 30 placebo recipients (34.5%) were censored from analysis. In an analysis of solicited and unsolicited adverse events reported in Study 1, the most common adverse reactions (defined as adverse events assessed as definitely, possibly, or probably related to Investigational Product by the investigator) reported by ≥3% of REBYOTA recipients, and at a rate greater than that reported by placebo recipients, were abdominal pain, (8.9%), diarrhea (7.2%), abdominal distention (3.9%), flatulence (3.3%), and nausea (3.3%) (Table 1).

Table 1: Adverse Reactions [Adverse reactions were defined as solicited and unsolicited adverse events that were assessed as definitely, possibly or probably related to treatment by the study investigator.] reported by ≥3% of REBYOTA recipients, and at a rate greater than that reported by placebo recipients, within 8 weeks after receipt of REBYOTA or placebo (Study 1).
Adverse Reaction | REBYOTA N=180 n (%) | Placebo N=87 n (%)
Abdominal Pain | 16 (8.9) | 6 (6.9)
Diarrhea | 13 (7.2) | 3 (3.4)
Abdominal distension | 7 (3.9) | 2 (2.3)
Flatulence | 6 (3.3) | 0
Nausea | 6 (3.3) | 1 (1.1)

Most adverse reactions occurred during the first 2 weeks after treatment. After this, the proportion of patients with adverse reactions declined in subsequent 2-week intervals. Beyond 2 weeks after treatment only a few single adverse reactions were reported. Most adverse drug reactions were mild to moderate in severity. No life-threatening adverse reaction was reported.

Serious Adverse Reactions

In a pooled analysis of the 5 clinical studies, 10.1% (60/595) of REBYOTA recipients (1 dose only) and 7.2% (6/83) of placebo recipients reported a serious adverse event within 6 months post last dose of investigational product. None of these events were considered related to the investigational product.

8 USE IN SPECIFIC POPULATIONS

8.1 Pregnancy

Risk Summary

REBYOTA is not absorbed systemically following rectal administration, and maternal use is not expected to result in fetal exposure to the drug.

8.2 Lactation

REBYOTA is not absorbed systemically by the mother following rectal administration, and breastfeeding is not expected to result in exposure of the child to REBYOTA.

8.4 Pediatric Use

Safety and effectiveness of REBYOTA in individuals younger than 18 years of age have not been established.

8.5 Geriatric Use

Of the 978 adults who received REBYOTA, 48.8% were 65 years of age and over (n=477), and 25.7% were 75 years of age and over (n=251). Data from clinical studies of REBYOTA are not sufficient to determine if adults 65 years of age and older respond differently than younger adults.

11 DESCRIPTION

REBYOTA (fecal microbiota, live – jslm) is an opaque fecal microbiota suspension for rectal administration. REBYOTA is manufactured from human fecal matter sourced from qualified donors. The human fecal matter is tested for a panel of transmissible pathogens. Donors do not have dietary restrictions with respect to potential food allergens. The fecal microbiota suspension is the filtrate generated by processing the fecal matter in a pre-defined ratio with a solution of polyethylene glycol (PEG) 3350 and saline. Each 150mL dose of REBYOTA contains between 1×10^8 and 5×10^10 colony forming units (CFU) per mL of fecal microbes including >1×10^5 CFU/mL of Bacteroides, and contains not greater than 5.97 grams of PEG3350 in saline.

12 CLINICAL PHARMACOLOGY

12.1 Mechanism of Action

The mechanism of action of REBYOTA has not been established.

13 NONCLINICAL TOXICOLOGY

No nonclinical toxicology studies were conducted.

14 CLINICAL STUDIES

The effectiveness of REBYOTA was evaluated using a Bayesian analysis of data from a randomized, double-blind, placebo-controlled, multicenter Phase 3 study (Study 1), which formally integrated treatment success rates from a placebo-controlled Phase 2 study (Study 2). Enrolled adults in both studies were 18 years of age or older and had a confirmed diagnosis of recurrent CDI (one or more episodes in Study 1; two or more episodes in Study 2) which was defined as diarrhea (passage of 3 or more loose bowel movements within a 24-hour period for 2 consecutive days) and a positive stool test for C. difficile toxin or toxigenic C. difficile, or had at least two episodes of severe CDI resulting in hospitalization within the last year. Enrolled adults were required to have completed at least 10 consecutive days of antibiotic therapy and have their CDI under control (<3 unformed/loose, i.e., Bristol Stool Scale type 6-7, stools/day for 2 consecutive days). A minimum of 24 hours to a maximum of 72 hours (Study 1) or 24 hours to a maximum of 48 hours (Study 2) antibiotic washout period was required prior to administration of the assigned study treatment. In Study 1, enrolled adults were randomized 2:1 to a single dose of REBYOTA or placebo respectively. In Study 2, randomization was 1:1:1 to receive two doses of REBYOTA, two doses of placebo, or one dose of REBYOTA and one dose of placebo, administered 7±2 days apart. Only data from the REBYOTA one-dose group and the placebo group are described below and were integrated in the Bayesian analysis.

In the integrated efficacy analysis set, the demographic profile and baseline recurrent CDI characteristics of treated adults were similar in the REBYOTA and placebo groups. In Study 1, a total of 262 adults were randomized and treated, of which 177 adults received REBYOTA and 85 received placebo. Adults had a mean age of 60.1 years with 45.4% of adults 65 years of age or older, were mainly white (92.0%) and female (69.1%). In this study, 32.8% of adults received REBYOTA or placebo for their first recurrence of CDI. In Study 1, 87.4% of adults had received vancomycin alone prior to treatment. In Study 2, 39 adults received one dose of REBYOTA and one dose of placebo and 43 adults received two doses of placebo. Adults in these two groups had a mean age of 59.8 years with 42.7% of adults 65 years of age or older, were mainly white (97.6%) and female (63.4%). In this study, 89.0% of adults had received vancomycin prior to treatment.

Treatment success was defined as the absence of CDI diarrhea within 8 weeks of blinded treatment. CDI diarrhea was defined as the passage of ≥ 3 unformed/loose stools in ≤ 24 hours for at least 2 consecutive days and a positive stool test for the presence of C difficile toxin at the time of the diarrhea.

In the Bayesian analysis, the estimated rate of treatment success was significantly higher in the REBYOTA group (70.6%) than in the Placebo group (57.5%) through 8 weeks after completing blinded treatment, resulting in a difference of 13.1 percentage points (95% Credible Interval: 2.3, 24.0) which corresponds to a 99.1% posterior probability that REBYOTA is superior to Placebo (Table 2).

Table 2: Efficacy Results: Treatment Success at 8 weeks Post-Treatment (mITT Population [mITT includes all randomized subjects excluding: 1) those who withdrew prior to treatment; 2) those in whom treatment was attempted but not completed; 3) those who discontinued from the study prior to evaluation of treatment outcome for the primary endpoint if the reason for exit was not related to CDI symptoms.])
Parameter | REBYOTA Mean (95% CrI) | Placebo Mean (95% CrI) | Treatment Effect (REBYOTA – Placebo) Mean (95% CrI)
Model-Estimated Treatment Success (%) | 70.6 (64.1, 76.8) | 57.5 (48.1, 67.1) | 13.1 (2.3, 24.0)
Posterior Probability of Superiority | - | - | 0.991 [Pre-defined threshold was 0.975]
CrI=credible interval

Study 1 evaluated sustained clinical response which was defined as treatment success at 8 weeks and no CDI event through 6 months after the last dose during the blinded period. The difference in sustained clinical response rate (9.1%; 95% CI: -3.6%, 21.7%) was not statistically significant between the REBYOTA (65.5%) and the placebo groups (56.5%).

16 HOW SUPPLIED/STORAGE AND HANDLING

16.1 How Supplied

REBYOTA and the administration set are shipped together in a box. Each box may contain up to 6 cartons of REBYOTA and up to 6 administration sets. Each carton of REBYOTA (NDC 55566-9800-2) contains a single dose.

16.2 Storage and Handling

REBYOTA contains live microorganisms. It is important to follow the storage requirements.

Upon Receipt:

Store the REBYOTA carton in an ultracold freezer (-60°C to -90°C, -76°F to -130°F). Alternatively, store in a refrigerator (2°C to 8°C, 36°F to 46°F) for up to 5 days (including thaw time). Do not refreeze REBYOTA after thawing.

Store the administration set at 10°C to 34°C (50°F to 93°F). DO NOT store the administration set in the freezer.

Before Using:

Prior to use, thaw REBYOTA completely by placing carton in a refrigerator (2°C to 8°C, 36°F to 46°F) for approximately 24 hours. Do not refreeze REBYOTA after thawing.

Dispose of all components in medical waste.

17 PATIENT COUNSELING INFORMATION

Inform patients that REBYOTA is manufactured from human fecal matter and may contain food allergens.

Inform patients to notify their physician if persistent diarrhea, defined as 3 or more loose bowel movements within a 24-hour period for 2 consecutive days, returns following REBYOTA administration.

Patients should not take any oral antibiotic therapy for up to 8 weeks after administration of REBYOTA unless directed by their physician.

Manufactured for Ferring Pharmaceuticals
by Rebiotix, Inc. Roseville, MN 55113

US License No. 2112

Ferring, the Ferring Pharmaceuticals logo are registered trademarks of Ferring B.V. REBYOTA is a trademark of Ferring B.V.

9009000002

PRINCIPAL DISPLAY PANEL - 150 mL Bag Carton

FERRING
PHARMACEUTICALS

NDC 55566-9800-2

1 single-dose
Rx Only

fecal microbiota, live-jslm
REBYOTA™

For rectal administration only.

Store and thaw in this carton.

Store the REBYOTA carton in an ultracold freezer
(-60°C to -90°°C, -76°F to -130°F). Alternatively, store in a
refrigerator (2°C to 8°C, 36°F to 46°F) for up to 5 days
(including thaw time). Do not refreeze REBYOTA after thawing.

Before Using:

Prior to use, thaw REBYOTA completely by placing carton
in a refrigerator (2°C to 8°C, 36°F to 46°F) for approximately
24 hours. Do not refreeze REBYOTA after thawing.

Condensation is normal
after thawing.

Contents:
One inner carton containing
a suspension bag of a single
150 mL dose of REBYOTA.

Use with the Administration Set
provided in a separate carton.